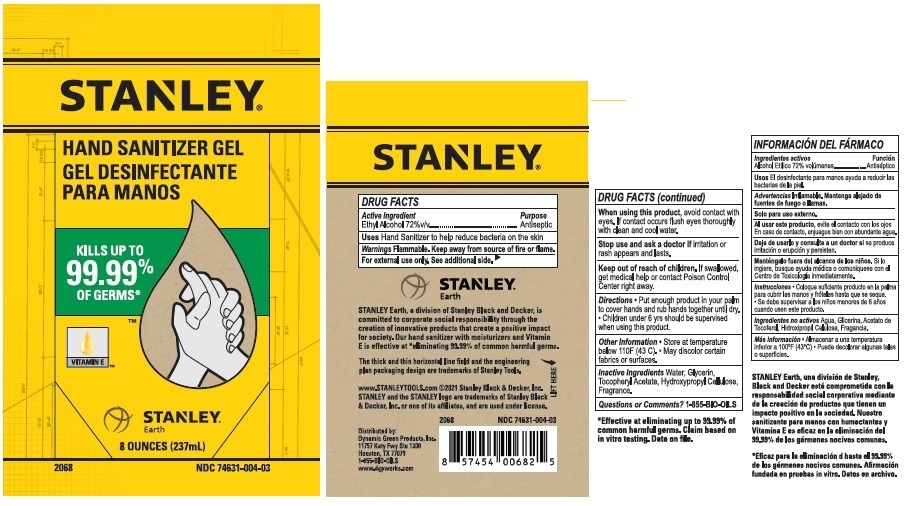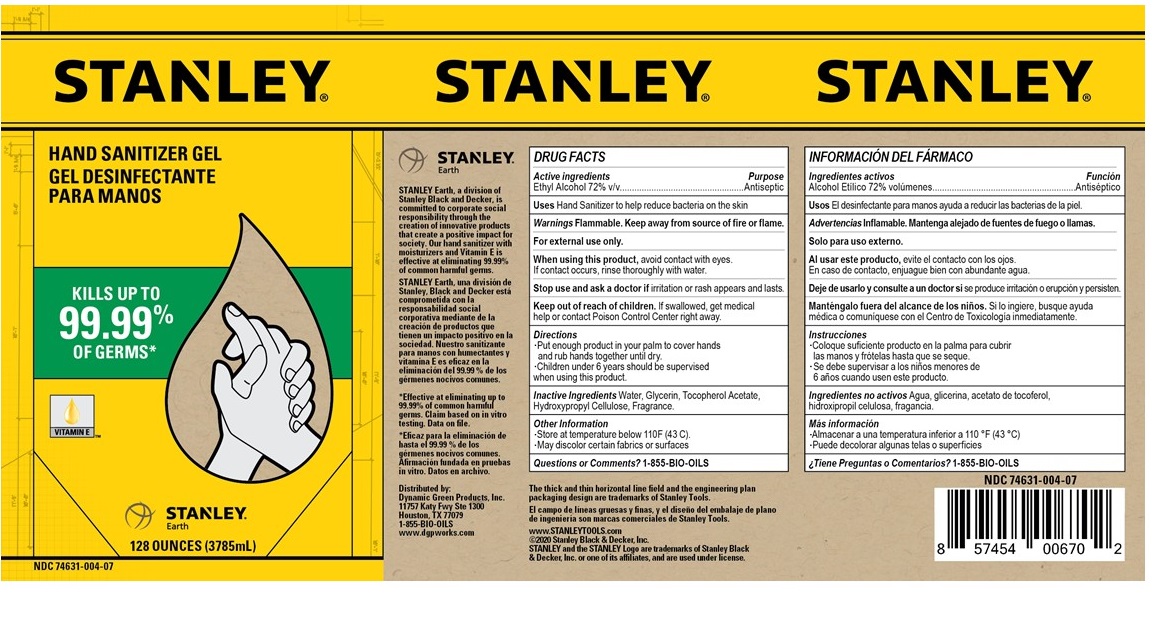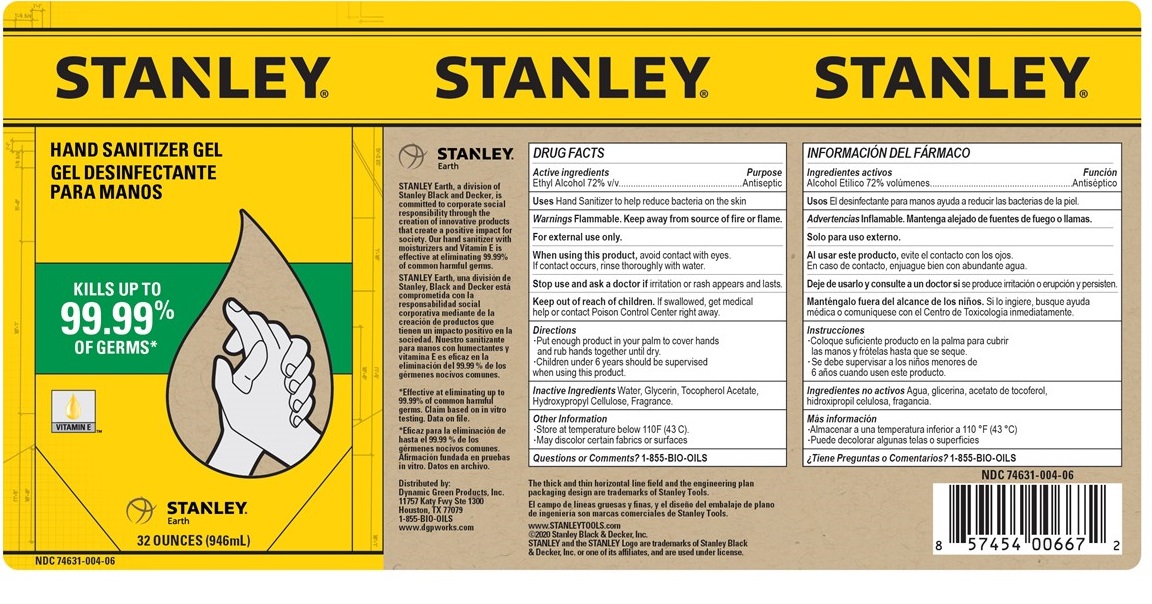 DRUG LABEL: Stanley Hand Sanitizer Gel
NDC: 74631-004 | Form: GEL
Manufacturer: Dynamic Green Products, Inc.
Category: otc | Type: HUMAN OTC DRUG LABEL
Date: 20210916

ACTIVE INGREDIENTS: ALCOHOL 72 mL/100 mL
INACTIVE INGREDIENTS: WATER; GLYCERIN; .ALPHA.-TOCOPHEROL ACETATE; HYDROXYPROPYL CELLULOSE (110000 WAMW); GRAPEFRUIT OIL

STANLEY HAND SANITIZER GEL

Active ingredient

Ethyl Alcohol 72% v/v

Purpose

Antiseptic

Uses

Hand Sanitizer to help reduce bacteria on the skin

Warnings

Flammable. Keep away from source of fire or flame.
For external use only. See additional side.

When using this product, avoid contact with eyes. If contact occurs flush eyes thoroughly with clean and cool water.

Stop use and ask a doctor If irritation or rash appears and lasts.

Keep out of reach of children. If swallowed, get medical help or contact a Poison Control Center right away.

Directions

* Put enough product in your palm to cover hands and rub hands together until dry.

* Children under 6 yrs should be supervised when using this product.

Other information

* Store at temperature below 110F (43 C). * May discolor certain fabrics or surfaces.

Inactive ingredients

Water, Glycerin, Tocopheryl Acetate, Hydroxypropyl Cellulose, Fragrance.

Questions or comments?

1-855-BIO-OILS

KILLS UP TO 99.99% OF GERMS*

Vitamin E

Stanley Earth, a division of Stanley Black and Decker, is committed to corporate social responsibility through the creation of innovative products that create a positive impact for society. Our hand sanitizer with moisturizers and Vitamin E is effective at *eliminating 99.99% of common harmful germs.

The thick and thin horizontal line field and the engineering plan packaging design are trademarks of Stanley Tools.

www.STANLEYTOOLS.com ©2020 Stanley Black & Decker, Inc.

STANLEY and the STANLEY logo are trademarks of Stanley Black & Decker, Inc. or one of its affiliates, and are used under license.

Distributed by:

Dynamic Green Products, Inc.

11757 Katy Fwy Ste 1300

Houston, TX 77079

1-855-BIO-OILS

www.dgpworks.com

*Effective at eliminating up to 99.99% of common harmful germs. Claim based on in vitro testing. Data on file.